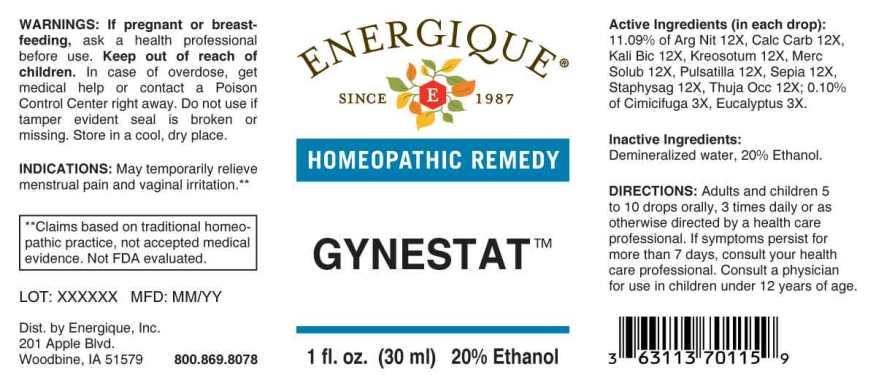 DRUG LABEL: Gynestat
NDC: 44911-0279 | Form: LIQUID
Manufacturer: Energique, Inc.
Category: homeopathic | Type: HUMAN OTC DRUG LABEL
Date: 20240802

ACTIVE INGREDIENTS: BLACK COHOSH 3 [hp_X]/1 mL; EUCALYPTUS GLOBULUS LEAF 3 [hp_X]/1 mL; SILVER NITRATE 12 [hp_X]/1 mL; OYSTER SHELL CALCIUM CARBONATE, CRUDE 12 [hp_X]/1 mL; POTASSIUM DICHROMATE 12 [hp_X]/1 mL; WOOD CREOSOTE 12 [hp_X]/1 mL; MERCURIUS SOLUBILIS 12 [hp_X]/1 mL; PULSATILLA PRATENSIS 12 [hp_X]/1 mL; SEPIA OFFICINALIS JUICE 12 [hp_X]/1 mL; DELPHINIUM STAPHISAGRIA SEED 12 [hp_X]/1 mL; THUJA OCCIDENTALIS LEAFY TWIG 12 [hp_X]/1 mL
INACTIVE INGREDIENTS: WATER; ALCOHOL

Drug Facts:

ACTIVE INGREDIENTS:

(in each drop): 11.09% of Argentum Nitricum 12X, Calcarea Carbonica 12X, Kali Bichromicum 12X, Kreosotum 12X, Mercurius Solubilis 12X, Pulsatilla (Pratensis) 12X, Sepia 12X, Staphysagria 12X, Thuja Occidentalis 12X; 0.10% of Cimicifuga Racemosa 3X, Eucalyptus Globulus 3X.

INDICATIONS:

May temporarily relieve menstrual pain and vaginal irritation.**

**Claims based on traditional homeopathic practice, not accepted medical evidence. Not FDA evaluated.

WARNINGS:

If pregnant or breast-feeding, ask a health professional before use.

Keep out of reach of children. In case of overdose, get medical help or contact a Poison Control Center right away.

Do not use if tamper evident seal is broken or missing. Store in a cool, dry place.

Keep out of reach of children. In case of overdose, get medical help or contact a Poison Control Center right away.

DIRECTIONS:

Adults and children 5 to 10 drops orally, 3 times daily or as otherwise directed by a health care professional. If symptoms persist for more than 7 days, consult your health care professional. Consult a physician for use in children under 12 years of age.

INDICATIONS:

May temporarily relieve menstrual pain and vaginal irritation.**

**Claims based on traditional homeopathic practice, not accepted medical evidence. Not FDA evaluated.

INACTIVE INGREDIENTS:

Demineralized water, 20% Ethanol.

QUESTIONS:

Dist. by Energique, Inc.

201 Apple Blvd

Woodbine, IA 51579 800-869-8078

PACKAGE LABEL DISPLAY:

ENERGIQUE

SINCE 1987

HOMEOPATHIC REMEDY

GYNESTAT

1 fL. oz. (30 ml)